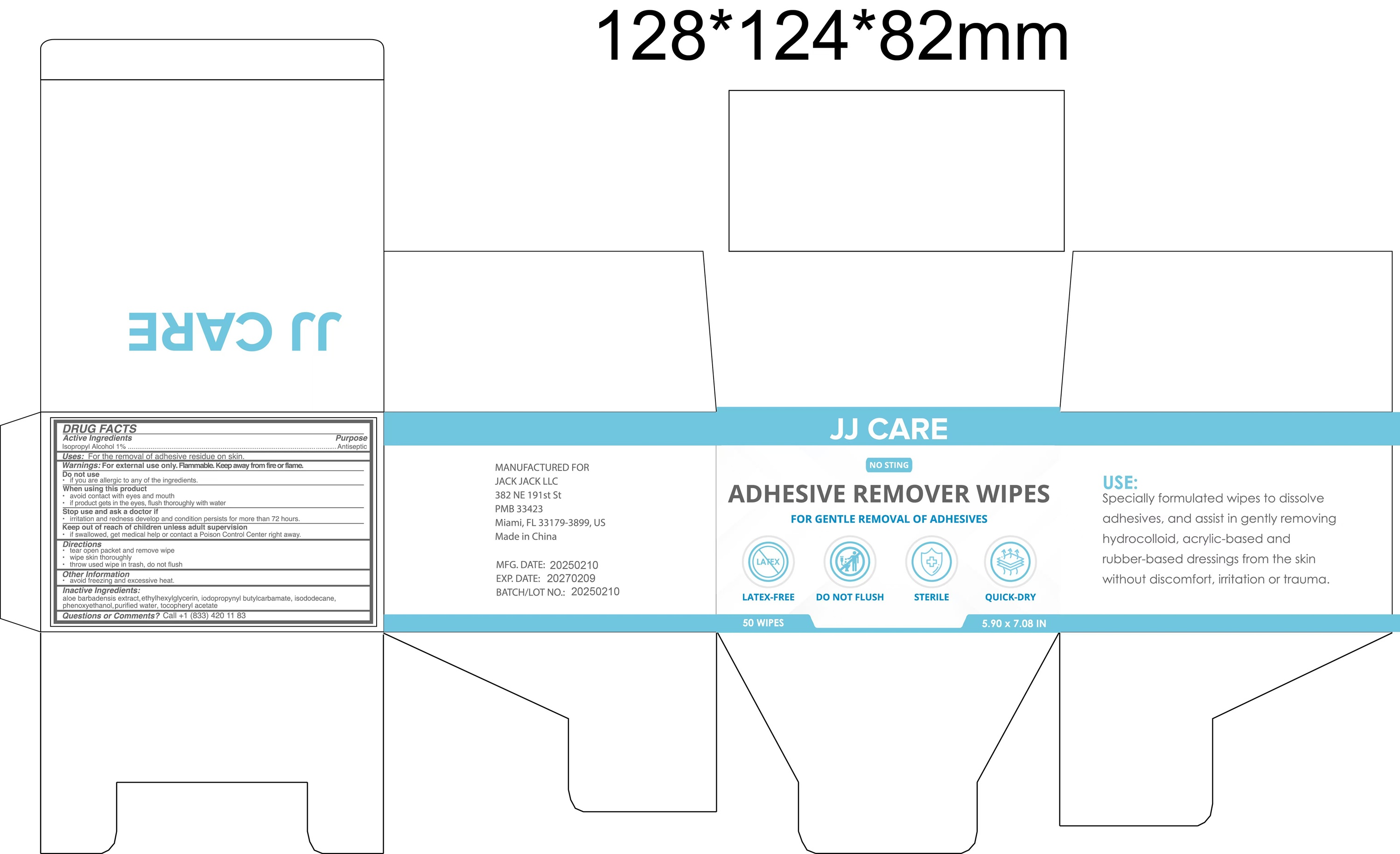 DRUG LABEL: Adhesive Remover Wipes
NDC: 85361-001 | Form: CLOTH
Manufacturer: SHAOXING KEQIAO HUNIAN HEALTH PRODUCTS CO.,LTD
Category: otc | Type: HUMAN OTC DRUG LABEL
Date: 20250315

ACTIVE INGREDIENTS: ISOPROPYL ALCOHOL 1 mL/100 mL
INACTIVE INGREDIENTS: ALPHA-TOCOPHEROL ACETATE; IODOPROPYNYL BUTYLCARBAMATE; FRAGRANCE LAVENDER & CHIA F-153480; ALOE BARBADENSIS LEAF; AQUA; ETHYLHEXYLGLYCERIN; ISODODECANE; PHENOXYETHANOL

Intended use

Intended use: For the removal of adhesive residue on skin.

Active Ingredients

Active Ingredients: Isopropyl Alcohol 1%

Warnings

Warnings: For external use only. Flammable. Keep away from fire or flame.

Do not use: If you are allergic to any of the ingredients.

When using this product

- avoid contact with eyes and mouth

- if product gets in

Stop use and ask a doctor if

- irritation and redness develop and condition persists for more than 72 hours.

Keep out of reach of children unless adult supervision

- if swallowed, get medical help or contact a Posion Control Center right away.

Directions

- tear open packet and remove wipe

- wipe skin thoroughly

- throw used wipe in trash, do not flush

Other information

- avoid freezing and excessive heat

Inactive Ingredients

Iodopropynyl Butylcarbamate, Phenoxyethanol, Ethylhexylglycerin, Isododecane, Tocopheryl Acetate, Aloe Barbadensis Extract,

Fragrance, Aqua

Questions or Comments

- Call +1 883 420 1183

Purpose

- For the removal of adhesive residue on skin

Dosage & Administration

- 1-2 pieces